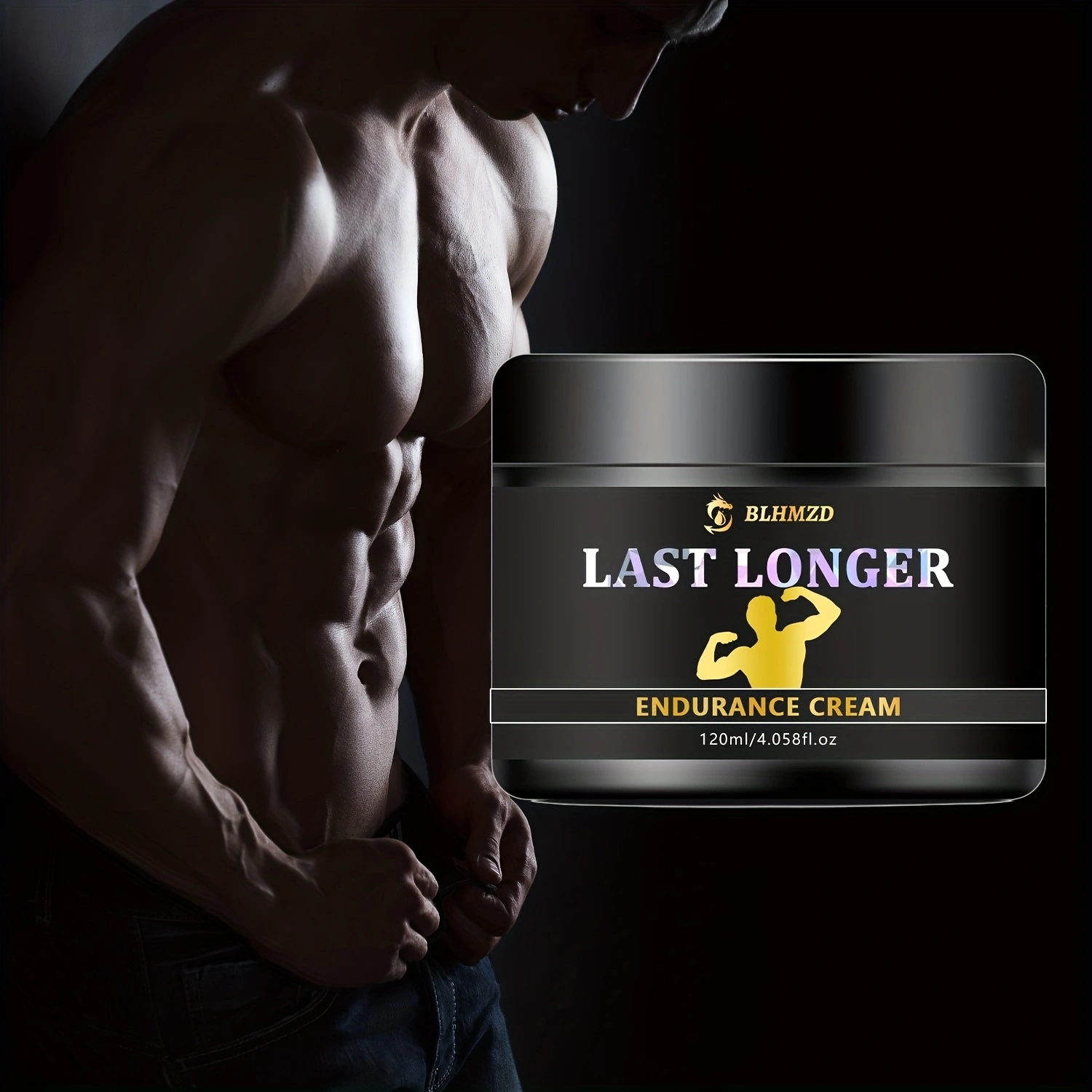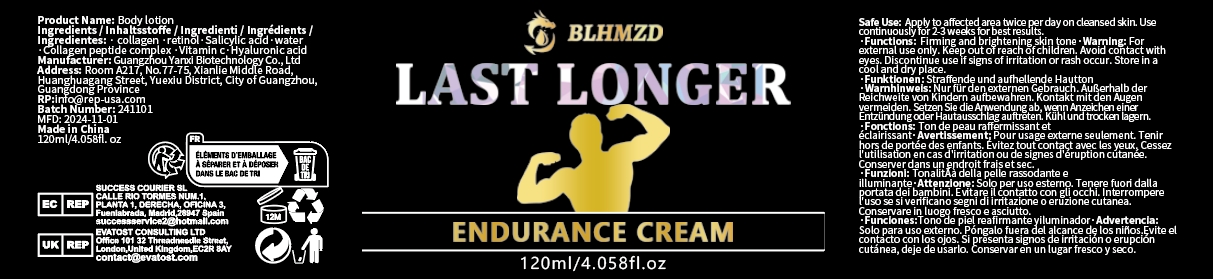 DRUG LABEL: bodylotion
NDC: 84025-312 | Form: CREAM
Manufacturer: Guangzhou Yanxi Biotechnology Co., Ltd
Category: otc | Type: HUMAN OTC DRUG LABEL
Date: 20250107

ACTIVE INGREDIENTS: HYALURONIC ACID 3 mg/120 mL; RETINOL 5 mg/120 mL
INACTIVE INGREDIENTS: WATER

WARNINGS

Keep out of children

DOSAGE AND ADMINISTRATION

Apply to affected area twice per day on cleansed skin.

INACTIVE INGREDIENT

Aqua

INDICATIONS AND USAGE

For daily skin care

Keep out of children

PURPOSE

Moisturizing skin